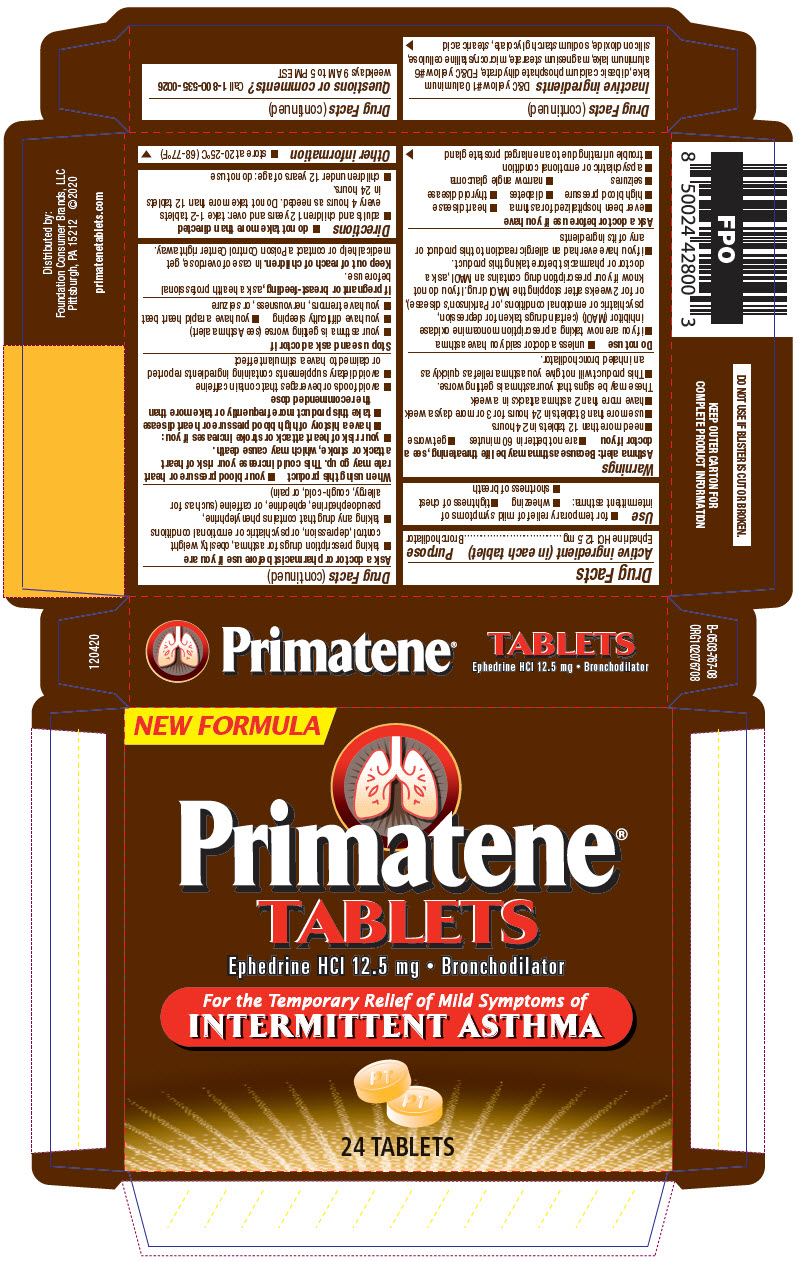 DRUG LABEL: Primatene
NDC: 80070-600 | Form: TABLET
Manufacturer: Foundation Consumer Brands
Category: otc | Type: HUMAN OTC DRUG LABEL
Date: 20241107

ACTIVE INGREDIENTS: EPHEDRINE HYDROCHLORIDE 12.5 mg/1 1
INACTIVE INGREDIENTS: SILICON DIOXIDE; DIBASIC CALCIUM PHOSPHATE DIHYDRATE; D&C YELLOW NO. 10 ALUMINUM LAKE; FD&C YELLOW NO. 6; MAGNESIUM STEARATE; MICROCRYSTALLINE CELLULOSE; SODIUM STARCH GLYCOLATE TYPE A POTATO; STEARIC ACID

Primatene®

Drug Facts

Active ingredient (in each tablet)

Ephedrine HCl 12.5 mg

Purpose

Bronchodilator

Use

- for temporary relief of mild symptoms of intermittent asthma:
  - wheezing
  - tightness of chest
  - shortness of breath

Warnings

Asthma alert

Because asthma may be life threatening, see a doctor if you

- are not better in 60 minutes
- get worse
- need more than 12 tablets in 24 hours
- use more than 8 tablets in 24 hours for 3 or more days a week
- have more than 2 asthma attacks in a week
  These may be signs that your asthma is getting worse.
- This product will not give you asthma relief as quickly as an inhaled bronchodilator.

Do not use

- unless a doctor said you have asthma
- if you are now taking a prescription monoamine oxidase inhibitor (MAOI) (certain drugs taken for depression, psychiatric or emotional conditions, or Parkinson's disease), or for 2 weeks after stopping the MAOI drug. If you do not know if your prescription drug contains an MAOI, ask a doctor or pharmacist before taking this product.
- if you have ever had an allergic reaction to this product or any of its ingredients

Ask a doctor before use if you have

- ever been hospitalized for asthma
- heart disease
- high blood pressure
- diabetes
- thyroid disease
- seizures
- narrow angle glaucoma
- a psychiatric or emotional condition
- trouble urinating due to an enlarged prostate gland

Ask a doctor or pharmacist before use if you are

- taking prescription drugs for asthma, obesity, weight control, depression, or psychiatric or emotional conditions
- taking any drug that contains phenylephrine, pseudoephedrine, ephedrine, or caffeine (such as for allergy, cough-cold, or pain)

When using this product

- your blood pressure or heart rate may go up. This could increase your risk of heart attack or stroke, which may cause death.
- your risk of heart attack or stroke increases if you:
  - have a history of high blood pressure or heart disease
  - take this product more frequently or take more than the recommended dose
- avoid foods or beverages that contain caffeine
- avoid dietary supplements containing ingredients reported or claimed to have a stimulant effect

Stop use and ask a doctor if

- your asthma is getting worse (see Asthma alert)
- you have difficulty sleeping
- you have a rapid heart beat
- you have tremors, nervousness, or seizure

PREGNANCY OR BREAST FEEDING

If pregnant or breast-feeding,ask a health professional before use.

Keep out of reach of children.In case of overdose, get medical help or contact a Poison Control Center right away.

Directions

- do not take more than directed
- adults and children 12 years and over: take 1-2 tablets every 4 hours as needed. Do not take more than 12 tablets in 24 hours.
- children under 12 years of age: do not use

Other information

- store at 20-25°C (68-77°F)

Inactive ingredients

D&C yellow #10 aluminum lake, dibasic calcium phosphate dihydrate, FD&C yellow #6 aluminum lake, magnesium stearate, microcrystalline cellulose, silicon dioxide, sodium starch glycolate, stearic acid

Questions or comments?

Call 1-800-535-0026weekdays 9 AM to 5 PM EST

Distributed by:
Foundation Consumer Brands, LLC
Pittsburgh, PA 15212

PRINCIPAL DISPLAY PANEL - 12.5 mg Tablet Blister Pack Carton

NEW FORMULA

Primatene®
TABLETS

Ephedrine HCl 12.5 mg • Bronchodilator

For the Temporary Relief of Mild Symptoms of
INTERMITTENT ASTHMA

24 TABLETS